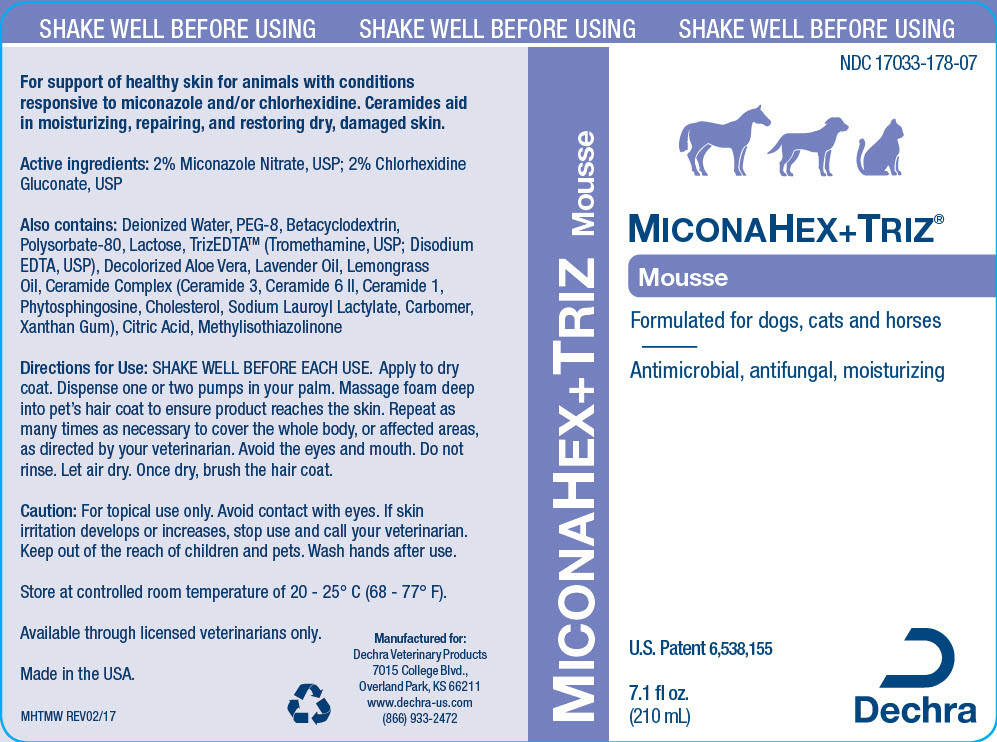 DRUG LABEL: MiconaHex Plus Triz Mousse
NDC: 17033-178 | Form: SPRAY, SUSPENSION
Manufacturer: Dechra Veterinary Products
Category: animal | Type: OTC ANIMAL DRUG LABEL
Date: 20211203

ACTIVE INGREDIENTS: Chlorhexidine Gluconate 20 mg/1 mL; MICONAZOLE NITRATE 20 mg/1 mL
INACTIVE INGREDIENTS: WATER; PEG-8 Laurate; BETADEX; POLYSORBATE 80; LACTOSE, UNSPECIFIED FORM; Polysorbate 20; WEST INDIAN LEMONGRASS OIL; LAVENDER OIL; CERAMIDE NP; CERAMIDE AP; CERAMIDE 1; PHYTOSPHINGOSINE; CHOLESTEROL; SODIUM LAUROYL LACTYLATE; CARBOMER HOMOPOLYMER, UNSPECIFIED TYPE; XANTHAN GUM; CITRIC ACID MONOHYDRATE; TROMETHAMINE; EDETATE DISODIUM ANHYDROUS

MiconaHex + Triz® Mousse

VETERINARY INDICATIONS

For support of healthy skin for animals with conditions responsive to miconazole and/or chlorhexidine. Ceramides aid in moisturizing, repairing, and restoring dry, damaged skin.

Active ingredients: 2% Miconazole Nitrate, USP; 2% Chlorhexidine Gluconate, USP

Also contains: Water, PEG-8, Cyclodextrin, Polysorbate-80, Lactose, TrizEDTA® (Tromethamine, USP; Disodium EDTA, USP), Lavender Oil, Lemongrass Oil, Ceramide Complex (Ceramide 3, Ceramide 6 II, Ceramide 1, Phytosphingosine, Cholesterol, Sodium Lauroyl Lactylate, Carbomer, Xanthan Gum), Polysorbate 20, Citric Acid

DOSAGE AND ADMINISTRATION

Directions for Use: SHAKE WELL BEFORE EACH USE. Apply to dry coat. Dispense one or two pumps in your palm. Massage foam deep into pet's hair coat to ensure product reaches the skin. Repeat as many times as necessary to cover the whole body, or affected areas, as directed by your veterinarian. Avoid the eyes and mouth. Do not rinse. Let air dry. Once dry, brush the hair coat.

WARNINGS

Caution: For topical use only. Avoid contact with eyes. If skin irritation develops or increases, stop use and call your veterinarian. Keep out of the reach of children and pets. Wash hands after use.

HOW SUPPLIED

STORAGE AND HANDLING

Store at room temperature.

Available through licensed veterinarians.

Made in the USA.

Manufactured for:
Dechra Veterinary Products
7015 College Blvd.,
Overland Park, KS 66211
www.dechra-us.com
(866) 933-2472

MHTMW REV03/20

PRINCIPAL DISPLAY PANEL - 210 mL Bottle Label

MICONAHEX+TRIZ Mousse

SHAKE WELL BEFORE USING

NDC 17033-178-07

MICONAHEX+TRIZ®
Mousse

Formulated for dogs, cats and horses

Antimicrobial, antifungal, antibiofilm,
moisturizing

7.1 fl oz.
(210 mL)

Dechra